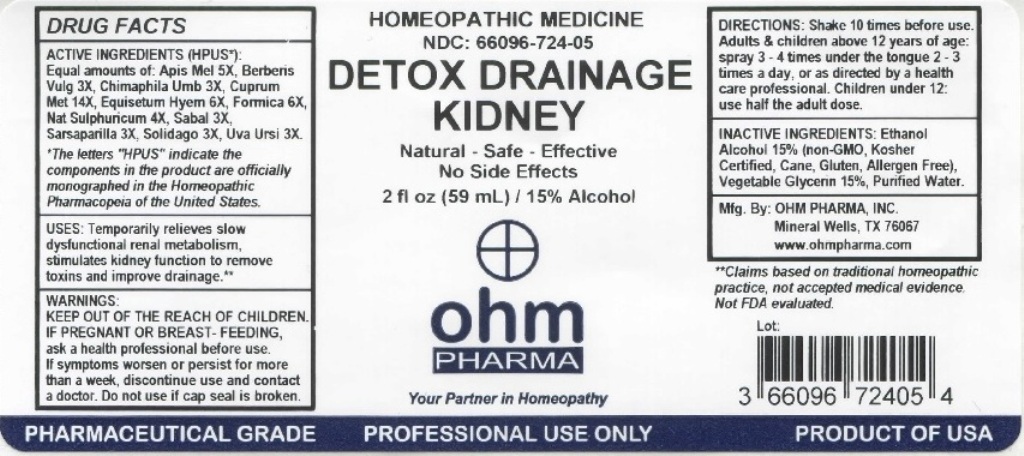 DRUG LABEL: Detox Drainage Kidney
NDC: 66096-724 | Form: LIQUID
Manufacturer: OHM PHARMA INC.
Category: homeopathic | Type: HUMAN OTC DRUG LABEL
Date: 20211229

ACTIVE INGREDIENTS: APIS MELLIFERA 5 [hp_X]/59 mL; BERBERIS VULGARIS ROOT BARK 3 [hp_X]/59 mL; CHIMAPHILA UMBELLATA 3 [hp_X]/59 mL; COPPER 14 [hp_X]/59 mL; EQUISETUM HYEMALE 6 [hp_X]/59 mL; FORMICA RUFA 6 [hp_X]/59 mL; SODIUM SULFIDE NONAHYDRATE 4 [hp_X]/59 mL; SAW PALMETTO 3 [hp_X]/59 mL; SARSAPARILLA 3 [hp_X]/59 mL; SOLIDAGO VIRGAUREA FLOWERING TOP 3 [hp_X]/59 mL; ARCTOSTAPHYLOS UVA-URSI LEAF 3 [hp_X]/59 mL
INACTIVE INGREDIENTS: ALCOHOL; AMINO ACIDS, CORN GLUTEN; WATER; GLYCERIN

OHM Detox Drainage Kidney

ACTIVE INGREDIENT

ACTIVE INGREDIENTS (HPUS*): Equal amounts of : Apis Mel 5X, Berber Vulg 3X, Chimaphila Umb 3X, Cuprum Met 14X, Equisetum Hyem6X, Formica 6X, Nat Sulphuricum 4X, Sabal 3X, Sarsaparilla 3X, Solidago 3X, Uva Ursi 3X.

*The letters "HPUS" indicate that the components in this product are officially monographed in the Homeopathic Pharmacopeia of the United States.

INDICATIONS AND USAGE

USES: Temporarily relieves slow dysfunctional renal metabolism, stimulates kidney function to remove toxins and improve drainage.**

**This statement has not been evaluated by the FDA. It is based on documented Homeopathic Materia Medica.

WARNINGS

WARNINGS: IF PREGNANT OR BREAST- FEEDING, ask a health professional before use. If symptoms worsen or persist for more than a week, discontinue use and contact a doctor.

- KEEP OUT OF THE REACH OF CHILDREN.

DOSAGE AND ADMINISTRATION

DIRECTIONS: Shake 10 times before use. Adults & children above 12 years of age: spray 3-4 times under the tongue 2-3 times a day, or as directed by a health care professional. Children under 12 use half the adult dose.

Do not use if cap seal is broken.

INACTIVE INGREDIENT

INACTIVE INGREDIENTS: Ethanol Alcohol 15% (Non-GMO, Kosher Certified, Corn, Gluten, Allergen Free), Purified Water, Vegetable Glycerin 15%.

QUESTIONS

Mfg. By: OHM PHARMA, INC. Mineral Wells TX 76067. www.ohmpharma.com

PACKAGE LABEL

HOMEOPATHIC MEDICINE

NDC: 66096-724-05

DETOX DRAINAGE KIDNEY

Natural - Safe - Effective

No Side Effects

2 fl oz (59mL) / 15% Alcohol

PRODUCT OF USA

PURPOSE

Temporarily relieves slow dysfunctional renal metabolism.